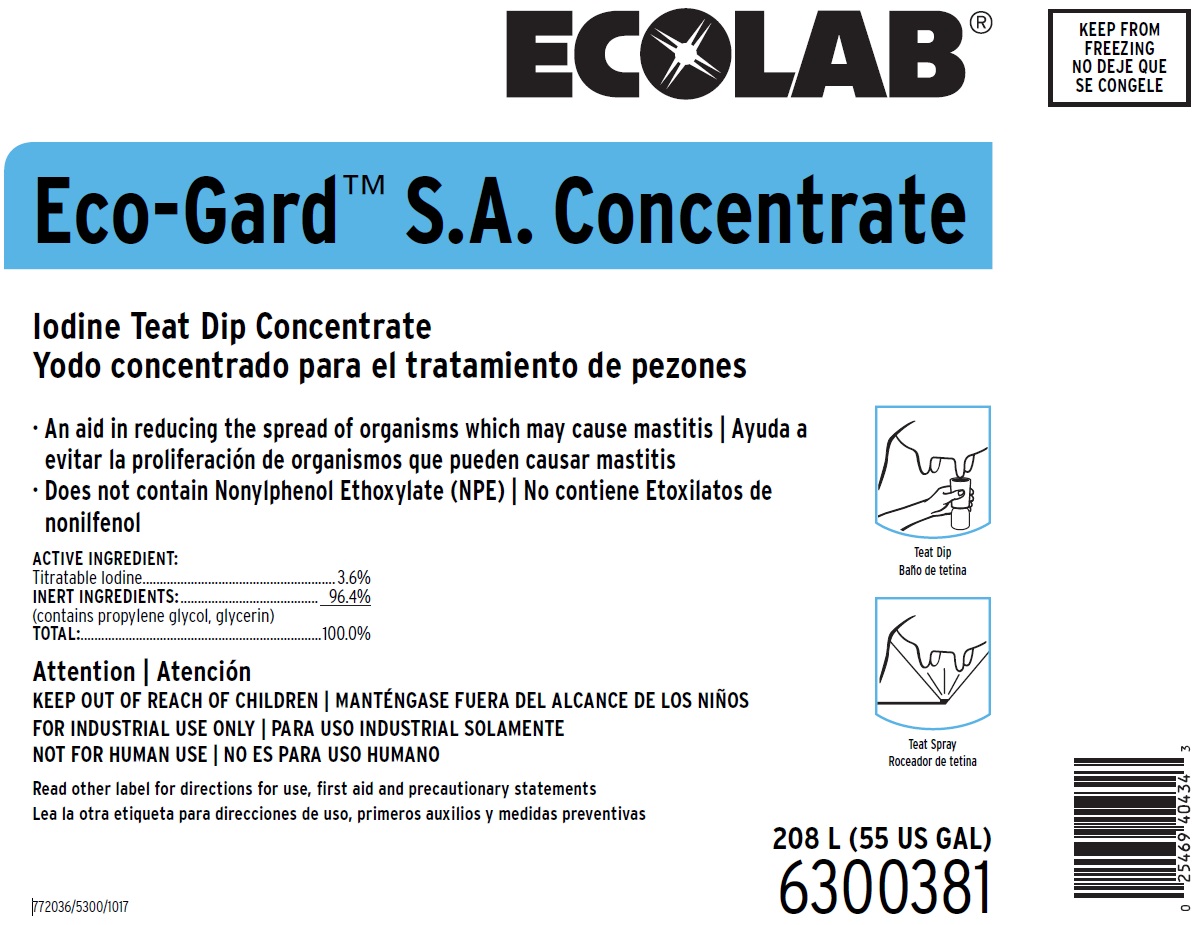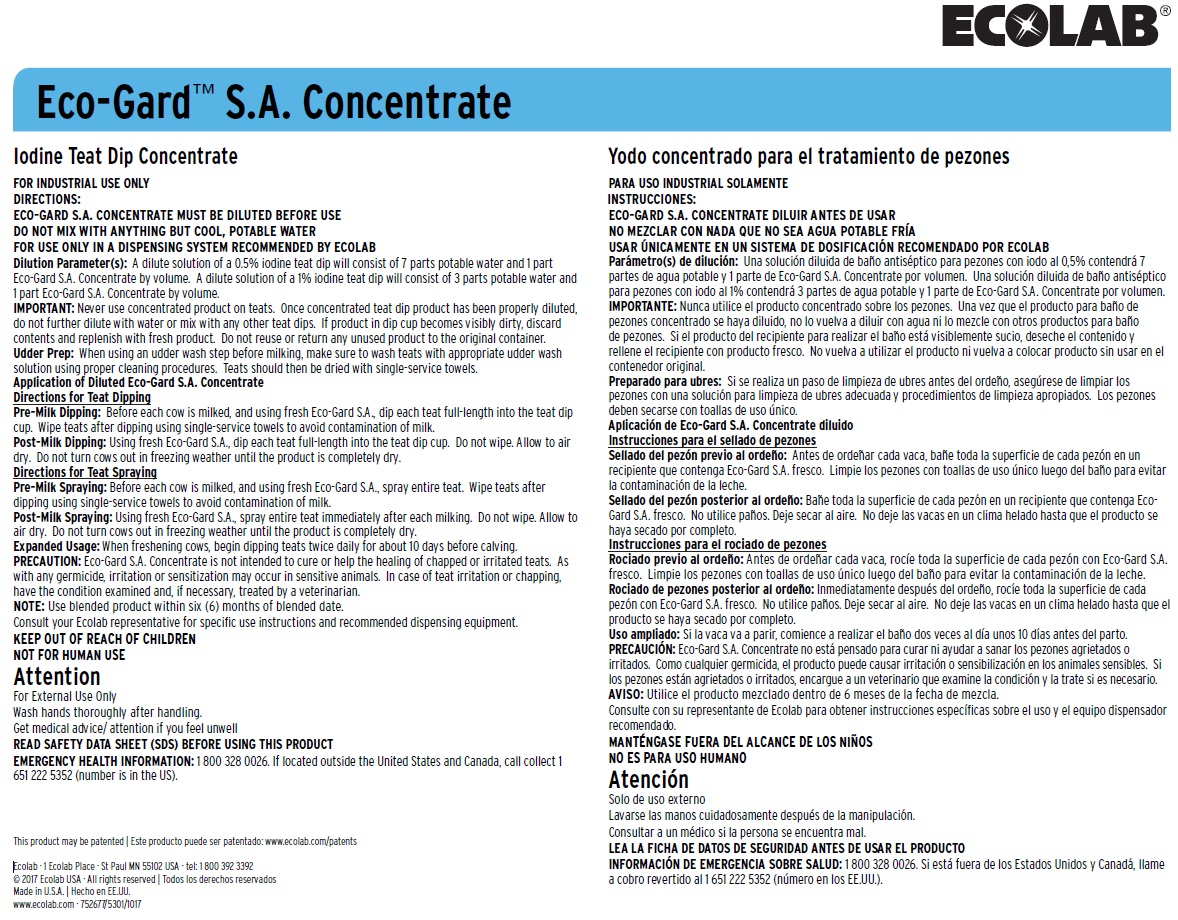 DRUG LABEL: Eco-Gard SA Concentrate
NDC: 47593-481 | Form: SOLUTION
Manufacturer: Ecolab Inc.
Category: animal | Type: OTC ANIMAL DRUG LABEL
Date: 20251012

ACTIVE INGREDIENTS: IODINE 36 mg/1 mL
INACTIVE INGREDIENTS: WATER

SAFE HANDLING WARNING

Attention

For External Use Only

Wash hands thoroughly after handling

Get medical advice/attention if you feel unwell

READ SAFETY DATA SHEET (SDS) BEFORE USING THIS PRODUCT

EMERGENCY HEALTH INFORMATION: 1 800 328 0026. If located outside the United States and Canada, call collect 1 651 222 5352 (number is in the US).

VETERINARY INDICATIONS

Iodine Teat Dip Concentrate

FOR INDUSTRIAL USE ONLY

DIRECTIONS:

ECO-GARD S.A. CONCENTRATE MUST BE DILUTED BEFORE USE

DO NOT MIX WITH ANYTHING BUT COOL, POTABLE WATER

FOR USE ONLY IN A DISPENSING SYSTEM RECOMMENDED BY ECOLAB

Dilution Parameter(s): A dilute solution of a 0.5% iodine teat dip will consist of 7 parts potable water and 1 part Eco-Gard S.A. Concentrate by volume. A dilute solution of a 1% iodine teat dip will consist of 3 parts potable water and 1 part Eco-Gard S.A. Concentrate by volume.

IMPORTANT: Never use concentrated product on teats. Once concentrated teat dip product has been properly diluted, do not further dilute with water or mix with any other teat dips. If product in dip cup becomes visibly dirty, discard contents and replenish with fresh product. Do not reuse or return any unused product to the original container.

Udder Prep: When using an udder wash step before milking, make sure to wash teats with appropriate udder wash solution using proper cleaning procedures. Teats should then be dried with single-service towels.

Application of Diluted Eco-Gard S.A. Concentrate

Directions for Teat Dipping

Pre-Milk Dipping: Before each cow is milked, and using fresh Eco-Gard S.A., dip each teat full-length into the teat dip cup. Wipe teats after dipping using single-service towels to avoid contamination of milk.

Post-Milk Dipping: Using fresh Eco-Gard S.A., dip each teat full-length into the teat dip cup. Do not wipe. Allow to air dry. Do not turn cows out in freezing weather until the product is completely dry.

Directions for Teat Spraying

Pre-Milk Spraying: Before each cow is milked, and using fresh Eco-Gard S.A., spray entire teat. Wipe teats after dipping using single-service towels to avoid contamination of milk.

Post-Milk Spraying: Using fresh Eco-Gard S.A., spray entire teat immediately after each milking. Do not wipe. Allow to air dry. Do not turn cows out in freezing weather until the product is completely dry.

Expanded Usage: When freshening cows, begin dipping teats twice daily for about 10 days before calving.

PRECAUTION: Eco-Gard S.A. Concentrate is not intended to cure or help the healing of chapped or irritated teats. As with any germicide, irritation or sensitization may occur in sensitive animals. In case of teat irritation or chapping, have the condition examined and, if necessary, treated by a veterinarian.

NOTE: Use blended product within six (6) months of blended date.

Consult your Ecolab representative for specific use instructions and recommended dispensing equipment.

OTHER SAFETY INFORMATION

Attention

KEEP OUT OF REACH OF CHILDREN

FOR INDUSTRIAL USE ONLY

NOT FOR HUMAN USE

Read other label for directions for use, first aid and precautionary statements

Principal Display Panel and Representative Label

ECOLAB®

Ecolab-Gard™ S.A. Concentrate

Iodine Teat Dip Concentrate

· An aid in reducing the spread of organisms which may cause mastitis

· Does not contain Nonylphenol Ethoxylate (NPE)

ACTIVE INGREDIENT:

Titratable Iodine........................................................3.6%

INERT INGREDIENTS:.......................................... 96.4%

(contains glycerin, propylene glycol)

TOTAL:...............................................................100.0%

208 L (55 US GAL)

6300381

772036/5300/1017

This product may be patented: www.ecolab.com/patents

Ecolab · 1 Ecolab Place · St Paul MN 55102 USA · tel: 1 800 392 3392

© 2017 Ecolab USA · All rights reserved

Made in U.S.A.

www.ecolab.com · 752677/5301/1017